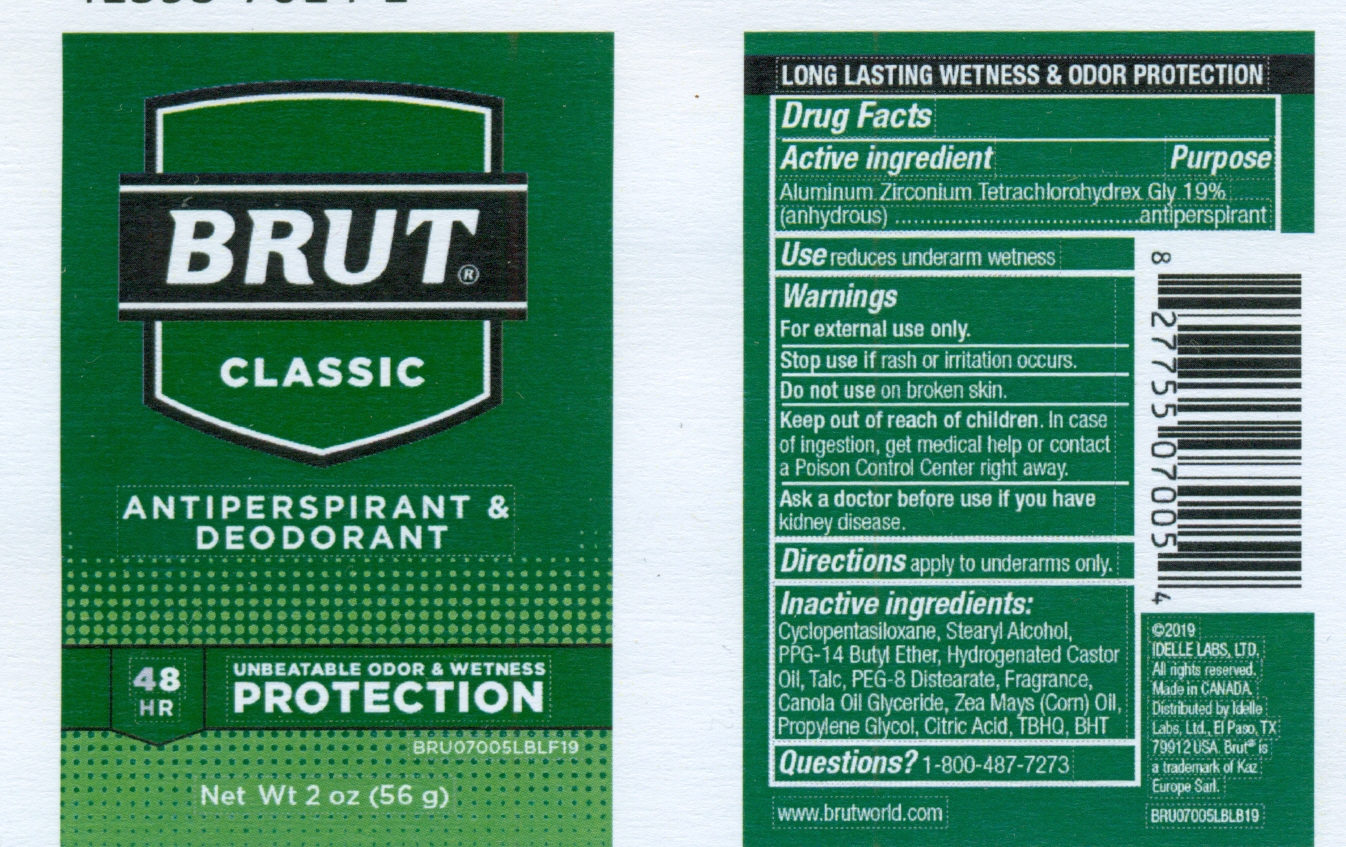 DRUG LABEL: Brut Classic Anti-perspirant and Deodorant
NDC: 41595-7014 | Form: STICK
Manufacturer: Idelle Labs, Ltd
Category: otc | Type: HUMAN OTC DRUG LABEL
Date: 20210820

ACTIVE INGREDIENTS: ALUMINUM ZIRCONIUM TETRACHLOROHYDREX GLY 19 g/100 g
INACTIVE INGREDIENTS: CYCLOMETHICONE 5; STEARYL ALCOHOL; PPG-14 BUTYL ETHER; HYDROGENATED CASTOR OIL; TALC; PEG-8 DISTEARATE; CANOLA OIL; CORN OIL; PROPYLENE GLYCOL; CITRIC ACID MONOHYDRATE; TERT-BUTYLHYDROQUINONE; BUTYLATED HYDROXYTOLUENE

BRUT CLASSIC ANTIPERSPIRANT AND DEODORANT

BRUT® CLASSIC

48H UNBEATABLE ODOR & WETNESS PROTECTION

ANTIPERSPIRANT+DEODORANT

Net Wt 2 oz (56 g)

LONG LASTING WETNESS & ODOR PROTECTION

DRUG FACTS

Active Ingredient

Aluminum Zirconium Tetrachlorohydrex Gly 19% (anhydrous)

Purpose

Antiperspirant

Use

Reduces underarm wetness

Warnings

For external use only.

Stop use if

Rash or irritation occurs.

Do not use

On broken skin.

Keep out of reach of children.

In case of ingestion, get medical help or contact a Poison Control Center right away.

Ask a doctor before use if you have

Kidney disease.

Directions

Apply to underarms only

Inactive Ingredients

Cyclopentasiloxane, Stearyl Alcohol, PPG-14 Butyl Ether, Hydrogenated Castor Oil, Talc, PEG-8 Distearate, Fragrance, Canola Oil Glyceride, Zea Mays (Corn) Oil, Propylene Glycol, Citric Acid, TBHQ, BHT

Questions?

Call 1-800-487-7273

www.brutworld.com

©IDELLE LABS, LTD.

All rights reserved.
Made in CANADA.
Distributed by Idelle Labs, Ltd., El Paso, TX 79912 USA.

Brut® is a trademark of Kaz Europe Sarl.